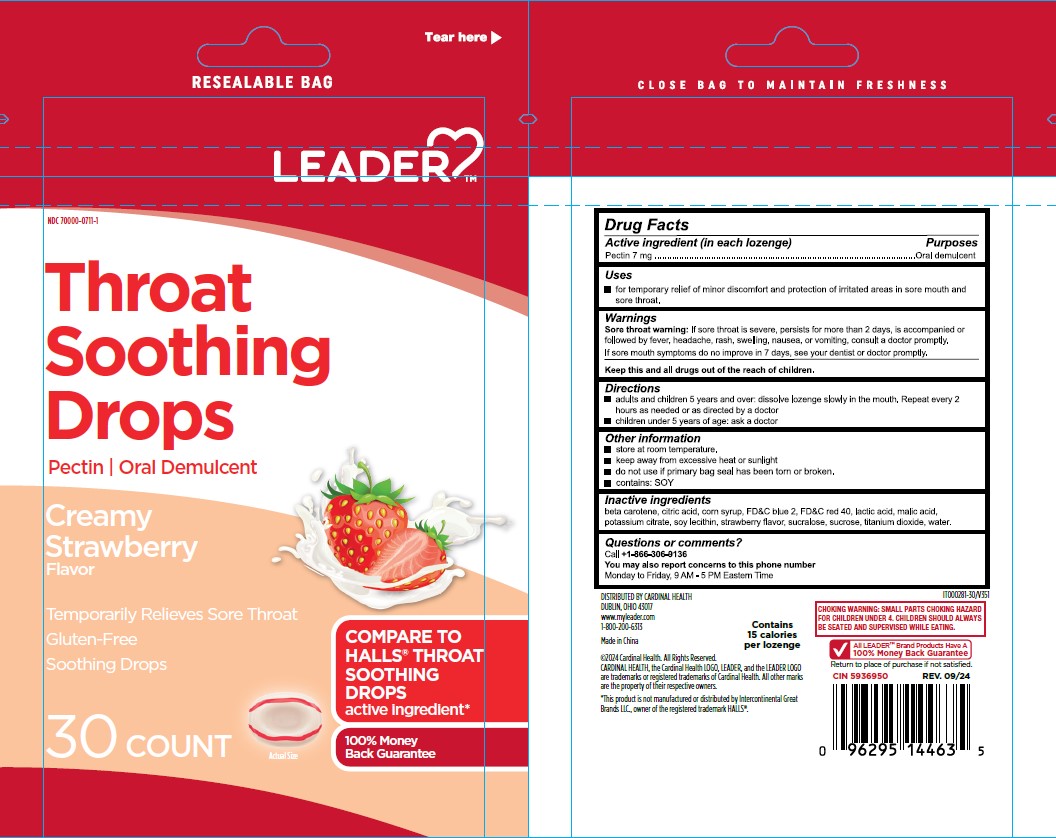 DRUG LABEL: Leader Throat Soothing Drops Creamy Strawberry
NDC: 83698-711 | Form: LOZENGE
Manufacturer: Xiamen Kang Zhongyuan Biotechnology Co., Ltd.
Category: otc | Type: HUMAN OTC DRUG LABEL
Date: 20251229

ACTIVE INGREDIENTS: PECTIN 7 mg/1 1
INACTIVE INGREDIENTS: BETA CAROTENE; CITRIC ACID MONOHYDRATE; FD&C BLUE NO. 2; FD&C RED NO. 40; CORN SYRUP; LACTIC ACID, UNSPECIFIED FORM; MALIC ACID; POTASSIUM CITRATE; SOYBEAN LECITHIN; SUCROSE; TITANIUM DIOXIDE; SUCRALOSE; WATER

Leader-Xiamen-MGC Creamy Strawberry Drop

Active ingredient (per drop)

Pectin 7 mg

Purposes

oral demulcent

Uses

For temporary relief of minor discomfort and protection of irritated areas in sore mouth and sore throat

Warnings

Sore throat warning:If sore throat is severe, persists for more than 2 days, is accompanied or followed by fever, headache, rash, swelling, nausea, or vomiting, consult a doctor promptly.

If sore mouth symptoms do not improve in 7 days, see your dentist or doctor promptly.

KEEP OUT OF REACH OF CHILDREN

Keep this and all drugs out of the reach of children.

Directions

• adults and children 5 years and over: dissolve lozenge slowly in the mouth. Repeat every 2 hours as needed or as directed by a doctor. • children under 5 years of age: ask a doctor.

Other information

• Store at room temperature • keep away from excessive heat or sunlight • do not use if primary bag seal has been torn or broken • contains: SOY.

Inactive ingredients

beta carotene, citric acid, corn syrup, FD&C blue 2, FD&C red 40, lactic acid, malic acid, potassium citrate, soy lecithin, strawberry flavor, sucrose, sucralose, titanium dioxide, water.

Questions?

call +1-866-306-9136 You may also report concerns to this phone number Monday to Friday 9AM-5PM Eastern Time